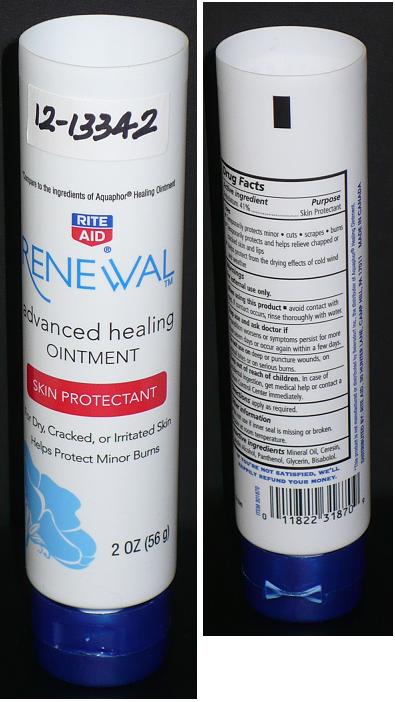 DRUG LABEL: RITE AID RENEWAL
NDC: 11822-3540 | Form: OINTMENT
Manufacturer: RITE AID CORPORATION
Category: otc | Type: HUMAN OTC DRUG LABEL
Date: 20120627

ACTIVE INGREDIENTS: PETROLATUM 41 g/100 g
INACTIVE INGREDIENTS: MINERAL OIL; CERESIN; LANOLIN ALCOHOLS; PANTHENOL; GLYCERIN; LEVOMENOL

Drug Facts

ACTIVE INGREDIENT

PETROLATUM 41%

PURPOSE

SKIN PROTECTANT

USES

TEMPORARILY PROTECTS MINOR CUTS, SCRAPES, BURNS. TEMPORARILY PROTECTS AND HELPS RELIEVE CHAPPED, CHAFED OR CRACKED SKIN AND LIPS. HELPS PROTECT FROM THE DRYING EFFECTS OF WIND AND COLD WEATHER.

WARNINGS

FOR EXTERNAL USE ONLY.

WHEN USING THIS PRODUCT

AVOID CONTACT WITH EYES. IF CONTACT OCCURS, RINSE THOROUGHLY WITH WATER.

STOP USE AND ASK DOCTOR IF

CONDITION WORSENS OR SYMPTOMS PERSIST FOR MORE THAN SEVEN DAYS OR OCCUR AGAIN WITHIN A FEW DAYS.

DO NOT USE

ON DEEP OR PUNCTURE WOUNDS, ON INFECTED AREAS OR ON SERIOUS BURNS.

KEEP OUT OF REACH OF CHILDREN

IN CASE OF ACCIDENTAL INGESTION, GET MEDICAL HELP OR CONTACT A POISON CONTROL CENTER IMMEDIATELY.

DIRECTIONS

APPLY AS REQUIRED.

OTHER INFORMATION

DO NOT USE IF INNER SEAL IS MISSING OR BROKEN. STORE AT ROOM TEMPERATURE.

INACTIVE INGREDIENTS

MINERAL OIL, CERESIN, LANOLIN ALCOHOL, PANTHENOL, GLYCERIN, BISABOLOL.